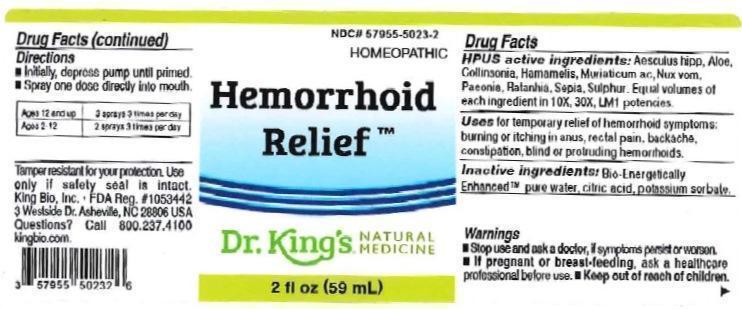 DRUG LABEL: Hemorrhoid Relief
NDC: 57955-5023 | Form: LIQUID
Manufacturer: King Bio Inc.
Category: homeopathic | Type: HUMAN OTC DRUG LABEL
Date: 20160627

ACTIVE INGREDIENTS: HORSE CHESTNUT 10 [hp_X]/59 mL; ALOE 10 [hp_X]/59 mL; COLLINSONIA CANADENSIS ROOT 10 [hp_X]/59 mL; HAMAMELIS VIRGINIANA ROOT BARK/STEM BARK 10 [hp_X]/59 mL; HYDROCHLORIC ACID 10 [hp_X]/59 mL; STRYCHNOS NUX-VOMICA SEED 10 [hp_X]/59 mL; PAEONIA OFFICINALIS ROOT 10 [hp_X]/59 mL; KRAMERIA LAPPACEA ROOT 10 [hp_X]/59 mL; SEPIA OFFICINALIS JUICE 10 [hp_X]/59 mL; SULFUR 10 [hp_X]/59 mL
INACTIVE INGREDIENTS: ANHYDROUS CITRIC ACID; POTASSIUM SORBATE; WATER

Hemorrhoid Relief™

ACTIVE INGREDIENT

Drug Facts__________________________________________________________________________________________________________

HPUS active ingredients: Aesculus hippocastanum, Aloe socotrina, Collinsonia canadensis, Hamamelis virginiana, Muriaticum acidum, Nux vomica, Paeonia officinalis, Ratanhia, Sepia, Sulphur. Equal volumes of each ingredient in 10X, 30X, LM1 potencies.

INDICATIONS AND USAGE

Uses for temporary relief of hemorrhoid symptoms: burning or itching in anus, rectal pain, backache, constipation, blind or protruding hemorrhoids.

Inactive Ingredients:

Bio-Energetically Enhanced™ pure water, citric acid and potassium sorbate.

Warnings

- Stop use and ask your doctor if symptoms persist or worsen.
- If pregnant or breast-feeding, ask a healthcare professional before use.

- Keep out of reach of children.

Directions

- Initially, depress pump until primed.
- Spray one dose directly into mouth.
- Ages 12 and up: 3 sprays 3 times per day.
- Ages 2-12: 2 sprays 3 times per day.

OTHER SAFETY INFORMATION

Tamper resistant for your protection. Use only if safety seal is intact.

PURPOSE

Uses for temporary relief of hemorrhoid symptoms:

- burning or itching in anus
- rectal pain
- backache
- constipation
- blind or protruding hemorrhoids